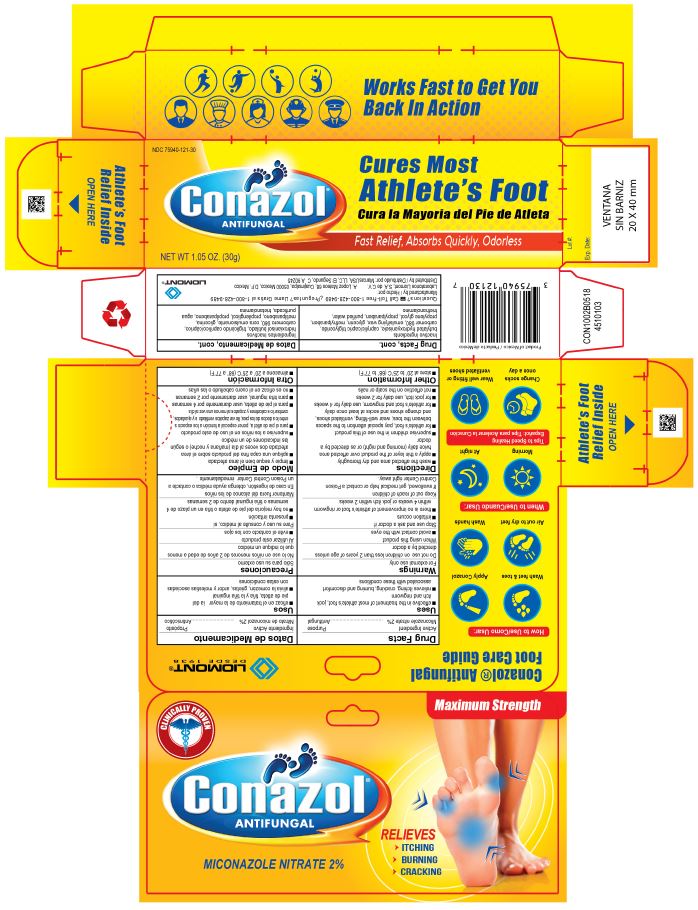 DRUG LABEL: Conazol
NDC: 75940-121 | Form: CREAM
Manufacturer: MarcasUSA LLC
Category: otc | Type: HUMAN OTC DRUG LABEL
Date: 20190115

ACTIVE INGREDIENTS: MICONAZOLE NITRATE 20 mg/1 g
INACTIVE INGREDIENTS: BUTYLATED HYDROXYANISOLE; TRICAPRIN; CARBOMER HOMOPOLYMER TYPE C; GLYCERIN; METHYLPARABEN; PROPYLENE GLYCOL; PROPYLPARABEN; WATER; TROLAMINE

Conazol Cream

Active Ingredients Purpose

Active ingredients
Miconazole nitrate 2%

Purpose
Antifungal

INDICATIONS AND USAGE

Uses

- effective in the treatment of most athlete's foot, jock
  itch and ringworm
- relieves itching, cracking, burning and discomfort
  associated with these conditions

Warnings

For external use only

Do not use

on children less than 2 years of age unless
directed by a doctor

When using this product

• avoid contact with the eyes

Stop use and ask a doctor if

- irritation occurs
- there is no improvement of athlete's foot or ringworm
  within 4 weeks or jock itch within 2 weeks

Keep out of reach of children

If swallowed, get medical help or contact a Poison
Control Center right away

Directions

- wash the affected area and dry thoroughly
- apply a thin layer of the product over affected area
  twice daily (morning and night) or as directed by a
  doctor
- supervise children in the use of this product
- for athlete's foot, pay special attention to the spaces
  between the toes; wear well-fitting, ventilated shoes,
  and change shoes and socks at least once daily
- for the athlete's foot and ringworm, use daily for 4 weeks
- for jock itch, use daily for 2 weeks
- not effective on the scalp or nails

Other Information

Store at 20° to 25°C (68° to 77°F)

INACTIVE INGREDIENT

Drug Facts, cont.

Inactive Ingredients

butylated hidroxyanisole, caprylic/capic triglyceride,
carbomer 980, emulsifying wax, glycerin, methylparaben,
propylene glycol, propylparaben, purified water,
triethanolamine

Questions? Call Toll-Free 1-800-428-9489 ¿Preguntas? Llame gratis al 1-800-428-9489
Manufactured by / Hecho Por

Laboratorios Liomont, S.A. de C.V. A, Lopez Mateos 68, Cuajimalpa, 05000 Mexico, D.F. Mexico.
Distributed by / Distribuido por: MarcasUSA, LLC, El Segundo CA 90245

Datos de Medicamento

ACTIVE INGREDIENT

Ingrediente Activo
Nitrato de miconazol 2%

Propósito
Antimicótico

Usos

- eficaz en el tratamiento de la mayoría del pie de atleta y la tiña inguinal
- alivia la comezón, grietas, ardor y molestias asociadas con estas condiciones

Precauciones

Sólo para uso externo

No lo use

en niños menores de 2 años de edad a menos
que lo indique un médico

Al utilizar este producto

- evite el contacto con los ojos

Pare su uso consulte al médico, si

- presenta irritación
- no hay mejoria del pie de atleta o tiña en un plazo de 4
  semanas o tiña inguinal dentro de 2 semanas

Mantener fuera del alcance de los niños.

En caso de ingestión, obtenga ayuda médica o contacte a
un Poison Control Center inmediatamente.

Modo de Empleo

- limpie y seque bien el área afectada
- aplique una capa fina del producto sobre el área
  afectada dos veces al diá (mañana y noche) o según
  las indicaciones de un médico
- supervise a los niños en el uso de este producto
- para el pie de atleta, poner especial atención a los espacios
  entre los dedos de los pies, llevar zapatos ventilados y ajustados,
  cambiar los calcetines y zapatos al menos una vez al dia
- para el pie de atleta, usar diariamente por 4 semanas
- para tiña inguinal, usar diariamente por 2 semanas
- no es eficaz en el cuero cabelludo o las uñas

Otra información

- almacene a 20° a 25° C (68° a 77° F)

INACTIVE INGREDIENT

Datos de Medicamento, cont.

Ingredientes Inactivos

hidroxianisol butilado, triglicérido caprilico/cáprico,
carbomero 980, cera emulsionante, glicerina,
metilparabeno, propilenglicol, propilparabeno, agua
purificada, trietanolamina

Questions? Call Toll-Free 1-800-428-9489 ¿Preguntas? Llame gratis al 1-800-428-9489
Manufactured by / Hecho Por

Laboratorios Liomont, S.A. de C.V. A, Lopez Mateos 68, Cuajimalpa, 05000 Mexico, D.F. Mexico.
Distributed by / Distribuido por: MarcasUSA, LLC, El Segundo CA 90245

PACKAGE LABEL.PRINCIPAL DISPLAY PANEL - 1.05 oz (30 g)

Works Fast to Get you Back In Action

NDC 75940-121-30

Conazol Antifungal

Cures Most Athlete's Foot

Cura la Mayoria del Ple de Atleta

Fast Relief, Absorbs Quickly, Odorless

NET WT
1.05 OZ (30g)